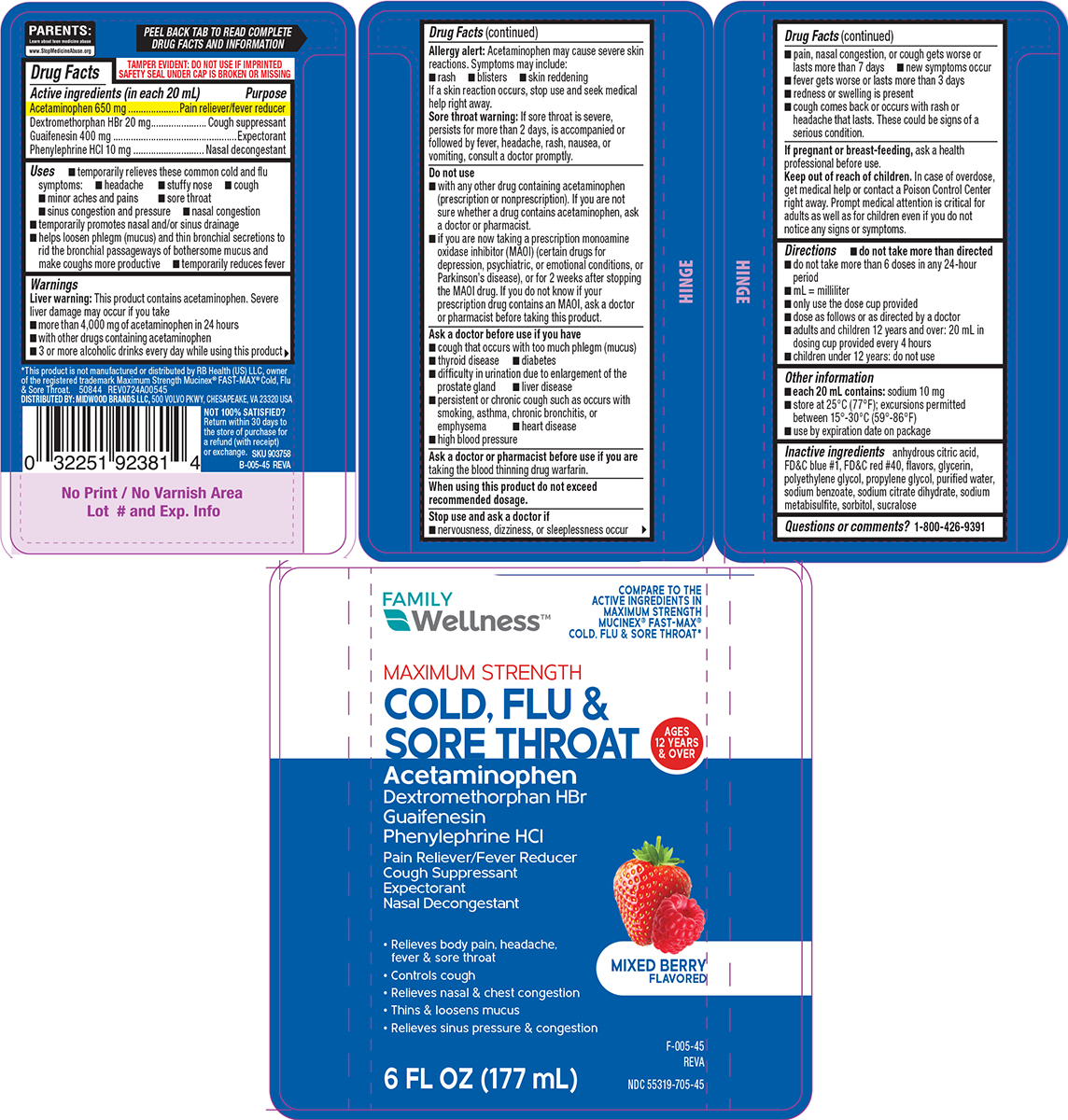 DRUG LABEL: Cold, Flu and Sore Throat
NDC: 55319-705 | Form: SOLUTION
Manufacturer: Family Dollar Services Inc
Category: otc | Type: HUMAN OTC DRUG LABEL
Date: 20260106

ACTIVE INGREDIENTS: ACETAMINOPHEN 650 mg/20 mL; DEXTROMETHORPHAN HYDROBROMIDE 20 mg/20 mL; GUAIFENESIN 400 mg/20 mL; PHENYLEPHRINE HYDROCHLORIDE 10 mg/20 mL
INACTIVE INGREDIENTS: ANHYDROUS CITRIC ACID; FD&C BLUE NO. 1; FD&C RED NO. 40; GLYCERIN; POLYETHYLENE GLYCOL, UNSPECIFIED; PROPYLENE GLYCOL; WATER; SODIUM BENZOATE; TRISODIUM CITRATE DIHYDRATE; SODIUM METABISULFITE; SORBITOL; SUCRALOSE

Family Wellness 44-005

Active ingredients (in each 20 mL)

Acetaminophen 650 mg
Dextromethorphan HBr 20 mg
Guaifenesin 400 mg
Phenylephrine HCl 10 mg

Purpose

Pain reliever/fever reducer
Cough suppressant
Expectorant
Nasal decongestant

Uses

- temporarily relieves these common cold and flu symptoms:
  - headache
  - stuffy nose
  - cough
  - minor aches and pains
  - sore throat
  - sinus congestion and pressure
  - nasal congestion
- temporarily promotes nasal and/or sinus drainage
- helps loosen phlegm (mucus) and thin bronchial secretions to rid the bronchial passageways of bothersome mucus and make coughs more productive
- temporarily reduces fever

Warnings

Liver warning: This product contains acetaminophen. Severe liver damage may occur if you take

- more than 4,000 mg of acetaminophen in 24 hours
- with other drugs containing acetaminophen
- 3 or more alcoholic drinks every day while using this product

Allergy alert: Acetaminophen may cause severe skin reactions. Symptoms may include:

- rash
- blisters
- skin reddening

If a skin reaction occurs, stop use and seek medical help right away.

Sore throat warning: If sore throat is severe, persists for more than 2 days, is accompanied or followed by fever, headache, rash, nausea, or vomiting, consult a doctor promptly.

Do not use

- with any other drug containing acetaminophen (prescription or nonprescription). If you are not sure whether a drug contains acetaminophen, ask a doctor or pharmacist.
- if you are now taking a prescription monoamine oxidase inhibitor (MAOI) (certain drugs for depression, psychiatric, or emotional conditions, or Parkinson’s disease), or for 2 weeks after stopping the MAOI drug. If you do not know if your prescription drug contains an MAOI, ask a doctor or pharmacist before taking this product.

Ask a doctor before use if you have

- cough that occurs with too much phlegm (mucus)
- thyroid disease
- high blood pressure
- difficulty in urination due to enlargement of the prostate gland
- liver disease
- diabetes
- persistent or chronic cough such as occurs with smoking, asthma, chronic bronchitis, or emphysema
- heart disease

Ask a doctor or pharmacist before use if you are

taking the blood thinning drug warfarin.

When using this product

do not exceed recommended dosage.

Stop use and ask a doctor if

- nervousness, dizziness, or sleeplessness occur
- pain, nasal congestion, or cough gets worse or lasts more than 7 days
- new symptoms occur
- fever gets worse or lasts more than 3 days
- redness or swelling is present
- cough comes back or occurs with rash or headache that lasts. These could be signs of a serious condition.

If pregnant or breast-feeding,

ask a health professional before use.

Keep out of reach of children.

In case of overdose, get medical help or contact a Poison Control Center right away. Prompt medical attention is critical for adults as well as for children even if you do not notice any signs or symptoms.

Directions

- do not take more than directed
- do not take more than 6 doses in any 24-hour period
- mL = milliliter
- only use the dose cup provided
- dose as follows or as directed by a doctor
- adults and children 12 years and over: 20 mL in dosing cup provided every 4 hours
- children under 12 years: do not use

Other information

- each 20 mL contains: sodium 10 mg
- store at 25°C (77°F); excursions permitted between 15°-30°C (59°-86°F)
- use by expiration date on package

Inactive ingredients

anhydrous citric acid, FD&C blue #1, FD&C red #40, flavors, glycerin, polyethylene glycol, propylene glycol, purified water, sodium benzoate, sodium citrate dihydrate, sodium metabisulfite, sorbitol, sucralose

Questions or comments?

1-800-426-9391

Principal display panel

FAMILY
Wellness™

COMPARE TO THE
ACTIVE INGREDIENTS IN
MAXIMUM STRENGTH
MUCINEX® FAST-MAX®
COLD, FLU & SORE THROAT*

MAXIMUM STRENGTH
COLD, FLU &
SORE THROAT

Acetaminophen
Dextromethorphan HBr
Guaifenesin
Phenylephrine HCl
Pain Reliever/Fever Reducer
Cough Suppressant
Expectorant
Nasal Decongestant

• Relieves body pain, headache,
fever & sore throat
• Controls cough
• Relieves nasal & chest congestion
• Thins & loosens mucus
• Relieves sinus pressure & congestion

AGES
12 YEARS
& OVER

MIXED BERRY
FLAVORED

NDC 55319-705-45

6 FL OZ (177 mL)

TAMPER EVIDENT: DO NOT USE IF IMPRINTED
SAFETY SEAL UNDER CAP IS BROKEN OR MISSING

PARENTS:
Learn about teen medicine abuse
www.StopMedicineAbuse.org

*This product is not manufactured or distributed by RB Health (US) LLC, owner
of the registered trademark Maximum Strength Mucinex® FAST-MAX® Cold, Flu
& Sore Throat. 50844 REV0724A00545

DISTRIBUTED BY: MIDWOOD BRANDS LLC, 500 VOLVO PKWY, CHESAPEAKE, VA 23320 USA

NOT 100% SATISFIED?
Return within 30 days to
the store of purchase for
a refund (with receipt)
or exchange.

Family Wellness 44-005